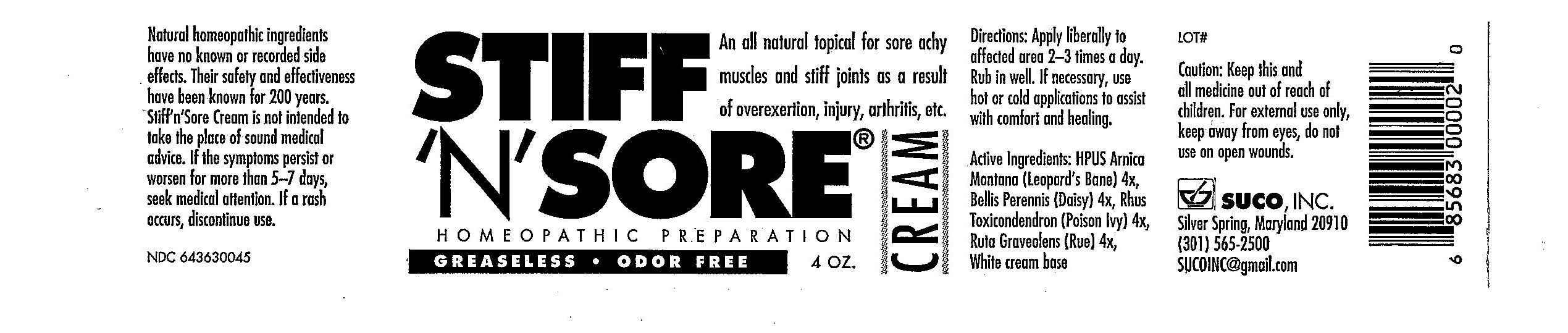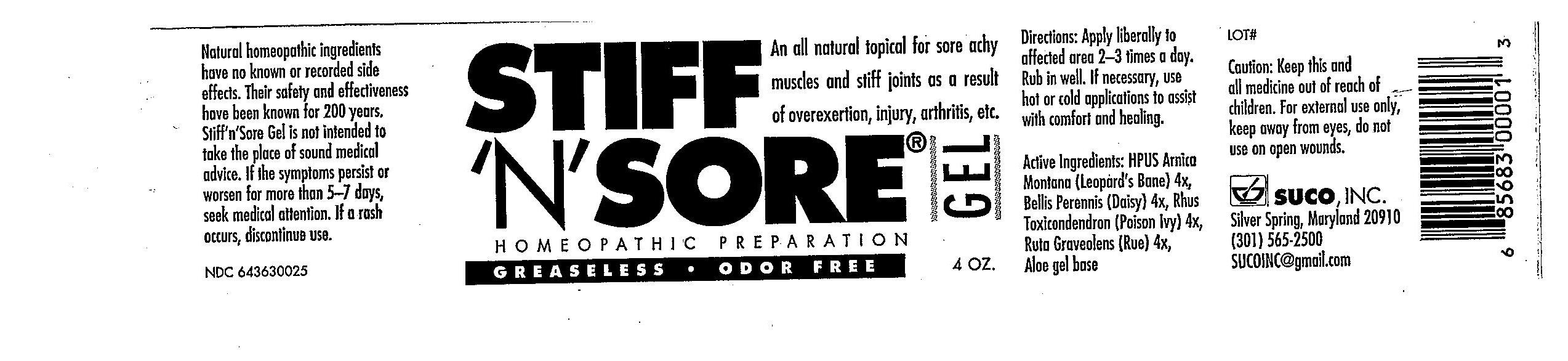 DRUG LABEL: Stiff n Sore
NDC: 64363-0025 | Form: GEL
Manufacturer: Suco Inc
Category: homeopathic | Type: HUMAN OTC DRUG LABEL
Date: 20241230

ACTIVE INGREDIENTS: ARNICA MONTANA 4 [hp_X]/480 g; BELLIS PERENNIS 4 [hp_X]/480 g; TOXICODENDRON PUBESCENS WHOLE 4 [hp_X]/480 g; RUTA GRAVEOLENS WHOLE 4 [hp_X]/480 g
INACTIVE INGREDIENTS: ALOE

KEEP OUT OF REACH OF CHILDREN

Caution: Keep this and all medicine out of reach of children. For external use only, keep away from eyes, do not use on open wounds.

DOSAGE AND ADMINISTRATION

Directions: Apply liberly to affected area 2-3 times a day, rub in well. If necessary, use hot or cold applications to assist with comfort and healing. For external use only, keep away from eyes, do not use on open wounds.

INDICATIONS AND USAGE

Homeopathic Preperation topical for sore achy muscles and stiff joints as a result of everexertion, injury, arthritis, etc.

WARNINGS

Caution: Keep this and all medications out of reach of children. For external use only, keep away from eyes, do not use on open skin.

INACTIVE INGREDIENT

aloe gel and shea butter

PURPOSE

a topical for sore achy muscles and stiff joints

ACTIVE INGREDIENT

Arnica Montana 4x

Bellis Perennis 4x

Rhus Toxicondendron 4x

Ruta Graveolens 4x